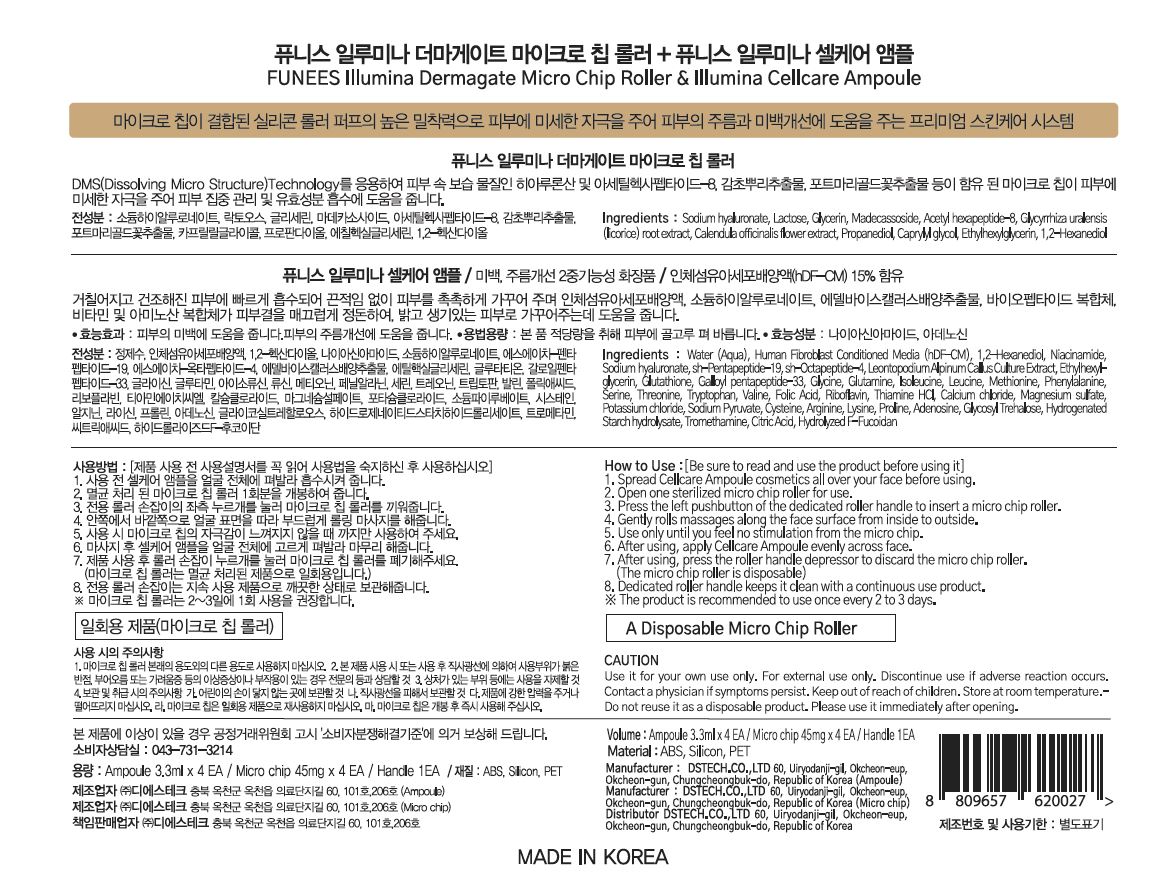 DRUG LABEL: FUNEES
NDC: 72910-0004 | Form: KIT | Route: TOPICAL
Manufacturer: DS TECH CO., LTD
Category: otc | Type: HUMAN OTC DRUG LABEL
Date: 20190802

ACTIVE INGREDIENTS: HYALURONATE SODIUM 6.14 g/100 mL; HYALURONATE SODIUM 0.8 g/100 mL
INACTIVE INGREDIENTS: WATER; GLYCERIN; WATER; ADENOSINE

Drug Facts

ACTIVE INGREDIENT

Sodium hyaluronate

INACTIVE INGREDIENT

- roller

Water
Human Fibroblast Conditioned Media
1,2-Hexanediol
Niacinamide
Sodium Hyaluronate
sh-Pentapeptide-19
sh-Octapeptide-4
Leontopodium Alpinum Callus Culture Extract
Ethylhexylglycerin
Glutathione
Galloyl Pentapeptide-33
Glycine
Glutamine
Isoleucine
Leucine
Methionine
Phenylalanine
Serine
Threonine
Tryptophan
Valine
Folic Acid
Riboflavin
Thiamine HCl
Calcium Chloride
Magnesium Sulfate
Potassium Chloride
Sodium Pyruvate
Cysteine
Arginine
Lysine
Proline
Adenosine
Glycosyl Trehalose
Hydrogenated Starch Hydrolysate
Tromethamine
Citric Acid
Hydrolyzed F-Fucoidan

- patch

Water
Acetyl hexapeptide-8 Water
Caprylyl glycol
Acetyl hexapeptide-8
Sodium hyaluronate
Cellulose gum
Lactose
Glycerin
Marigold Extract HD Water
Calendula officinalis flower extract
1,2-Hexanediol
Licorice Extract HD Water
Glycyrrhiza uralensis (licorice) root extract
1,2-Hexanediol
GH-815 Propanediol
Caprylyl glycol
Ethylhexyl glycerin
Madecassoside

PURPOSE

DMS (Dissolving Micro Structure) Technology Microchip gives minute skin stimulation to help skin concentrate and absorb active ingredients

keep out of reach of the children

INDICATIONS AND USAGE

spread water soluble cosmetics all over your face before using

open one sterilized micro chip roller for use

press the left pushbutton of the dedicated roller handle to insert a micro chip roller

gently rolls massages along the fact surface from inside to outside

use only until you feel no stimulation from the micro chip

after using, apply cosmetics evenly across face

after using, press the roller handle depressor to discard the micro chip roller (the micro chip roller is disposable)

dedicated roller handle keeps it clean with a continous use product

(this product is recommended to use one every 2 to 3 days)

WARNINGS

Use it for your own use only.

For external use only.

Discontinue use if adverse reaction occurs.

Contact a physician if symptoms persist.

Store at room temperature

.Do not reuse it as a disposable product.

Please use it immediately after opening.

DOSAGE AND ADMINISTRATION

for topical use only